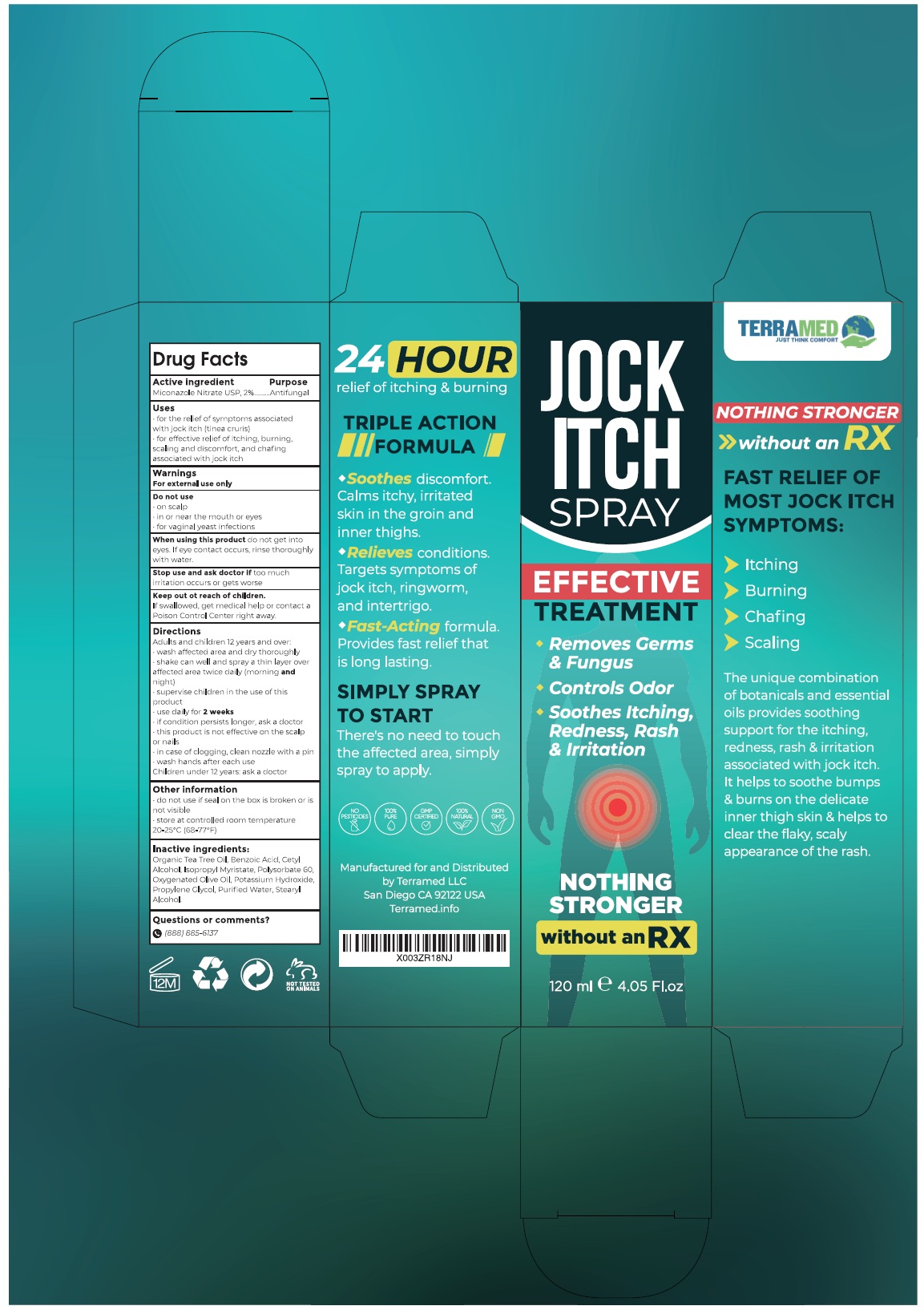 DRUG LABEL: Terramed Just Think Comfort Jock Itch Antifungal Treatment
NDC: 83004-020 | Form: LIQUID
Manufacturer: Rida LLC
Category: otc | Type: HUMAN OTC DRUG LABEL
Date: 20250306

ACTIVE INGREDIENTS: MICONAZOLE NITRATE 2 g/100 mL
INACTIVE INGREDIENTS: TEA TREE OIL; BENZOIC ACID; CETYL ALCOHOL; ISOPROPYL MYRISTATE; POLYSORBATE 60; OLIVE OIL; POTASSIUM HYDROXIDE; PROPYLENE GLYCOL; WATER; STEARYL ALCOHOL

Active Ingredient

Miconazole nitrate USP, 2%

Purpose

Antifungal

Uses

● for the relief of symptoms associated with jack itch (tinea cruris)

● for effective relief of itching, burning, scaling and discomfort and chafing associated with jock itch

Warnings

For external use only.

Do not use

- on scalp
- in or near the mouth or eyes
- for vaginal yeast infections

When using this product do not get into eyes. If eye contact occurs, rinse thoroughly with water.

Stop use and ask a doctor iftoo much irritation occurs or gets worse
Keep out of the reach of children.
If swallowed, get medical help or contact a Poison Control Center right away.

Directions

Adults and children 12 years and over:

- wash affected area and dry thoroughly
- shake can well and spray a thin layer over affected area twice daily (morning andnight)
- supervise children in the use of this product
- use daily for 2 weeks
- if condition persists longer, ask a doctor
- this product is not effective on the scalp or nails
- wash hands after each use
- in case of clogging, clean with a pin
- Children under 12 years: ask a doctor

Other information

- do not use if seal on the box is broken or is not visible.
- store at controlled room temperature 20-25°C (68-77°F)

Inactive ingredients

Organic tea tree oil, benzoic acid, cetyl alcohol, isopropyl myristate, polysorbate 60, olive oil, potassium hydroxide, propylene glycol, water, stearyl alcohol